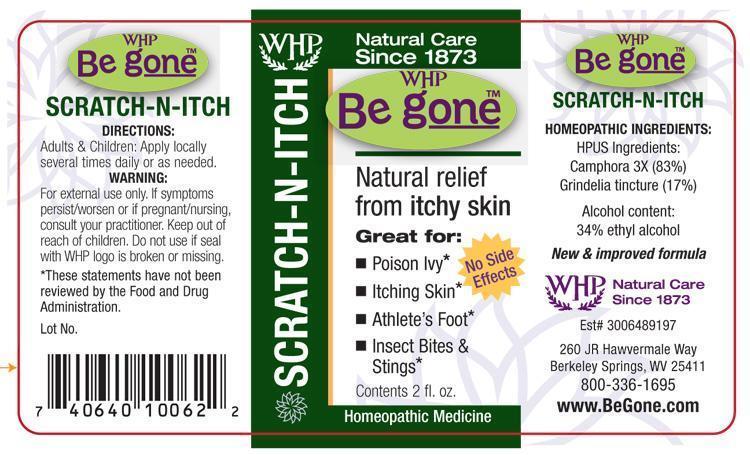 DRUG LABEL: WHP Be gone SCRATCH-N-ITCH
NDC: 68428-983 | Form: SPRAY
Manufacturer: Washington Homeopathic Products
Category: homeopathic | Type: HUMAN OTC DRUG LABEL
Date: 20130802

ACTIVE INGREDIENTS: GRINDELIA SQUARROSA FLOWERING TOP 1 [hp_X]/60 mL; CAMPHOR (NATURAL) 3 [hp_X]/60 mL
INACTIVE INGREDIENTS: ALCOHOL; WATER

DRUG FACTS

ACTIVE INGREDIENTS

GRINDELIA

CAMPHOR

USES

Relief from itchy skin.

KEEP OUT OF REACH OF CHILDREN

INDICATIONS

GRINDELIA Rash

CAMPHOR Coldness

STOP USE AND ASK DOCTOR

For external use only. If symptoms persist/worsen or if pregnant/nursing, consult your practitioner. Do not use if seal with WHP logo is broken or missing.

DIRECTIONS

Adults & Children: Apply locally several times daily or as needed.

INACTIVE INGREDIENTS

34% Ethyl alcohol

USP water